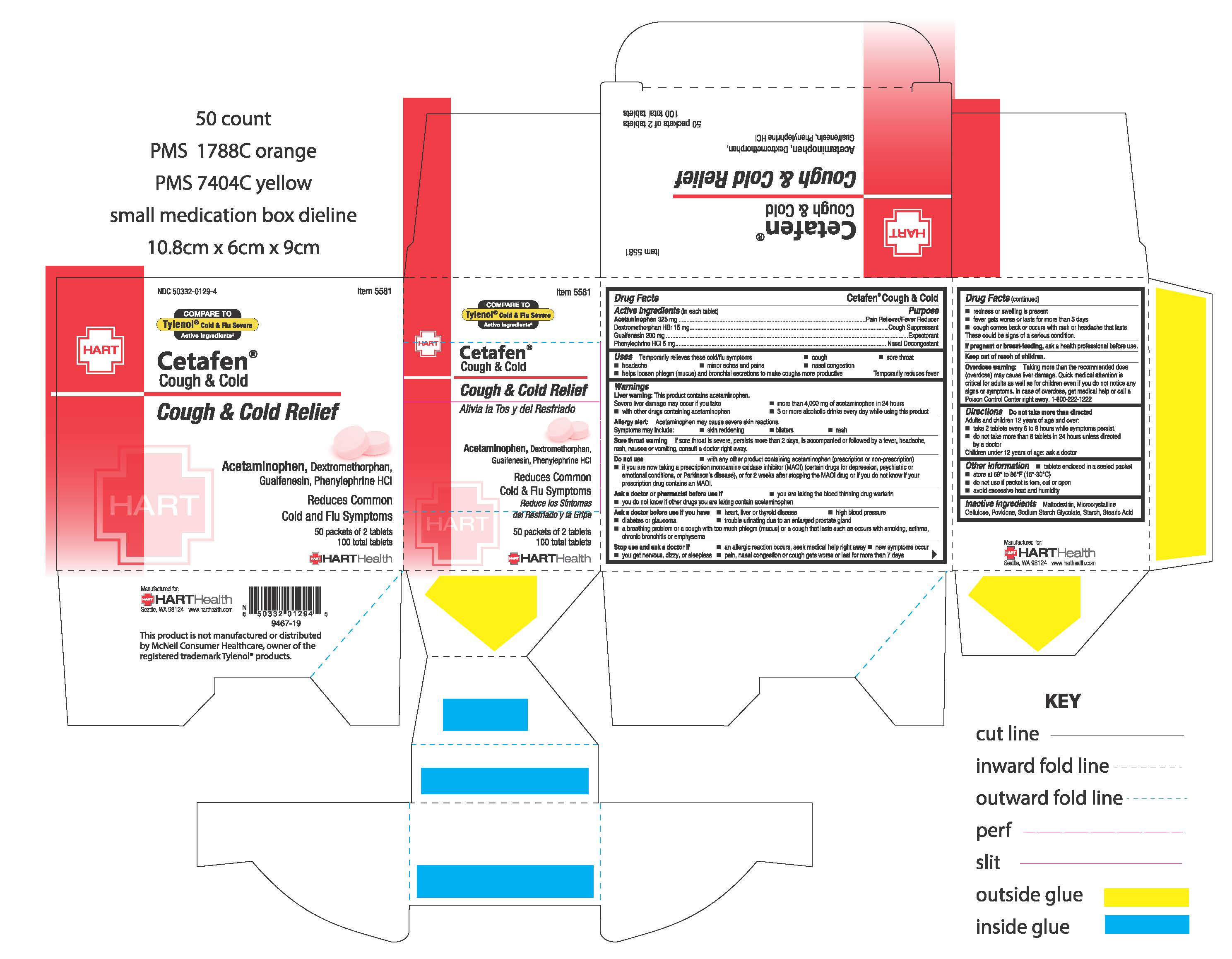 DRUG LABEL: CETAFEN COUGH AND COLD
NDC: 50332-0129 | Form: TABLET
Manufacturer: HART Health
Category: otc | Type: HUMAN OTC DRUG LABEL
Date: 20200605

ACTIVE INGREDIENTS: ACETAMINOPHEN 325 mg/1 1; DEXTROMETHORPHAN HYDROBROMIDE 15 mg/1 1; GUAIFENESIN 200 mg/1 1; PHENYLEPHRINE HYDROCHLORIDE 5 mg/1 1
INACTIVE INGREDIENTS: MALTODEXTRIN; MICROCRYSTALLINE CELLULOSE; POVIDONE; STEARIC ACID; STARCH, CORN; SODIUM STARCH GLYCOLATE TYPE A CORN

CETAFEN COUGH and COLD

Active Ingredients (in each tablet):

Acetaminophen 325 mg

Dextromethorphan HBr 15 mg

Guaifenesin 200 mg

Phenylephrine HCl 5 mg

Purpose:

Pain Reliever/Fever Reducer

Cough Suppressant

Expectorant

Nasal Decongestant

Uses:

Temporarily relieves these cold/flu symptoms

- cough
- sore throat
- headache
- minor aches and pains
- nasal congestion
- helps loosen phlegm (mucus) and bronchial secretions to make coughs more productive

Temporarily reduces fever

Warnings:

Liver warning: This product contains acetaminophen.

Severe liver damage may occur if you take

- more than 4,000 mg of acetaminophen in 24 hours
- with other drugs containing acetaminophen
- 3 or more alcoholic drinks every day while using this product

Allergy alert: Acetaminophen may cause severe skin reactions.

Symptoms may include:

- skin reddening
- blisters
- rash

Sore throat warning:

If sore throat is severe, persists more than 2 days, is accompanied or followed by a fever, headache, rash, nausea or vomiting, consult a doctor right away.

Do not use

- with any other product containing acetaminophen (prescription or non-prescription)
- if you are now taking a prescription monoamine oxidase inhibitor (MAOI)(certain drugs for depression, psychiatric or emotional conditions, or Pakinson's disease), or for 2 weeks after stopping the MAOI drug or if you do not know if your prescription drug contains an MAO.

Ask a doctor or pharmacist before use if

- you are taking the blood thinning drug warfarin
- you do not know if other drugs you are taking contain acetaminophen

Ask a doctor before use if you have

- heart, liver or thyroid desease
- high blood pressure
- diabetes or glaucoma
- trouble urinating due to an enlarged prostate gland
- a breathing problem or a cough with too much phlegm (mucus) or a cough that lasts such as occurs with smoking, asthma, chronic bronchitis or emphysema

Stop use and ask a doctor if

- an allergic reaction occurs, seek medical help right away
- new symptoms occur
- you get nervous, dizzy, or sleepless
- pain, nasal congestion or cough gets worse or last for more than 7 days
- redness or swelling is present
- fever gets worse or lasts for more than 3 days
- cough comes back or occurs with rash or headache that lasts

These could be signs of a serious condition.

PREGNANCY OR BREAST FEEDING

If pregnant or breast-feeding, ask a health professional before use.

Keep out of reach of children.

OVERDOSAGE

Overdose wasrning:

Taking more than the recommended dose (overdose) may cause liver damage. Quick medical attention is critical for adults as well as for children even if you do not notice any signs or symptoms. In case of overdose, get medical help or call a Poison Control Center right away. 1-800-222-1222

Directions:

Do not take more than directed.

Adults and children 12 years of age and over:

- take 2 tablets every 6 to 8 hours while symptoms persist.
- do not take more than 8 tablets in 24 horus unless directed by a doctor

Children under 12 years of age: ask a doctor

Inactive Ingredients:

Maltodextrin, Microcrystalline Cellulose, Povidone, Sodium Starch Glycolate, Starch, Stearic Acid